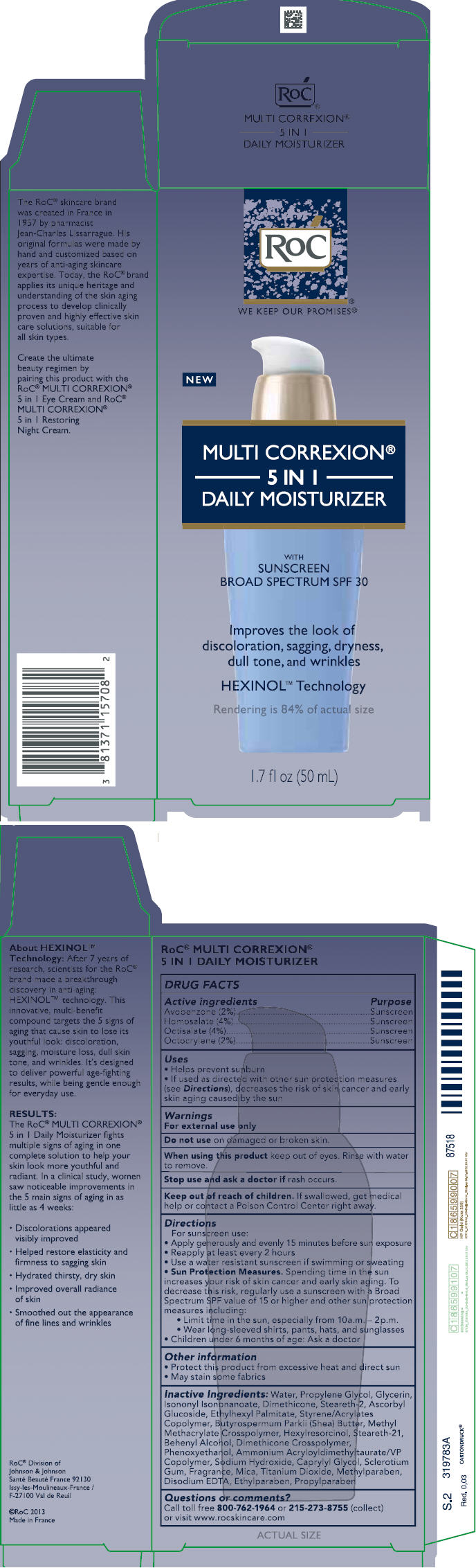 DRUG LABEL: ROC MULTI CORREXION 5 IN 1 DAILY MOISTURIZER SUNSCREEN BROAD SPECTRUM SPF30
NDC: 73496-002 | Form: LOTION
Manufacturer: ROC Skincare
Category: otc | Type: HUMAN OTC DRUG LABEL
Date: 20191204

ACTIVE INGREDIENTS: AVOBENZONE 20 mg/1 mL; HOMOSALATE 40 mg/1 mL; OCTISALATE 40 mg/1 mL; OCTOCRYLENE 20 mg/1 mL
INACTIVE INGREDIENTS: WATER; PROPYLENE GLYCOL; GLYCERIN; ISONONYL ISONONANOATE; DIMETHICONE; STEARETH-2; ASCORBYL GLUCOSIDE; ETHYLHEXYL PALMITATE; STYRENE/ACRYLAMIDE COPOLYMER (500000 MW); SHEA BUTTER; METHYL METHACRYLATE/GLYCOL DIMETHACRYLATE CROSSPOLYMER; HEXYLRESORCINOL; STEARETH-21; DOCOSANOL; DIMETHICONE CROSSPOLYMER (450000 MPA.S AT 12% IN CYCLOPENTASILOXANE); PHENOXYETHANOL; AMMONIUM ACRYLOYLDIMETHYLTAURATE/VP COPOLYMER; SODIUM HYDRIDE; CAPRYLYL GLYCOL; BETASIZOFIRAN; MICA; TITANIUM DIOXIDE; METHYLPARABEN; EDETATE DISODIUM ANHYDROUS; ETHYLPARABEN; PROPYLPARABEN

ROC MULTI CORREXION 5 IN 1 DAILY MOISTURIZER SUNSCREEN BROAD SPECTRUM SPF30

PACKAGE LABEL PRINCIPAL DISPLAY PANEL

OTC - PURPOSE

Active ingredientsPurposeAvobenzone (2%)SunscreenHomosalate (4%)SunscreenOctisalate (4%)SunscreenOctocrylene (2%)Sunscreen

OTC - KEEP OUT OF REACH OF CHILDREN

Keep out of reach of children. If swallowed, get medical help or contact a Poison Control Center right away

USES

Helps prevent sunburnif used as directed with other sun protection measures (see Directions), decreases the risk of skin cancer and early skin aging caused by the sun

WARNINGS

For external use only

Do not use on damaged or broken skin

When using this product keep out of eyes. Rinse with water to remove.

Stop use and ask a doctor if rash occurs

DIRECTIONS

For sunscreen use:apply generously and evenly15 minutes before sun exposurereapply at least every 2 hoursuse a water resistant sunscreen if swimming or sweatingSun Protection Measures. Spending time in the sun increases your risk of skin cancer and early skin aging. To decrease this risk, regularly use a sunscreen with a Broad Spectrum SPF value of 15 or higher and other sun protection measures including:limit time in the sun, especially from 10 a.m. – 2 p.m.wear long-sleeved shirts, pants, hats, and sunglasseschildren under 6 months of age: Ask a doctor

INACTIVE INGREDIENTS

Water, Propylene Glycol, Glycerin, Isononyl Isononanoate, Dimethicone, Steareth-2, Ascorbyl Glucoside, Ethylhexyl Palmitate, Styrene/Acrylates Copolymer, Butyrospermum Parkii (Shea) Butter, Methyl Methacrylate Crosspolymer, Hexylresorcinol, Steareth-21, Behenyl Alcohol, Dimethicone Crosspolymer, Phenoxyethanol, Ammonium Acryloyldimethyltaurate/VP Copolymer, Sodium Hydroxide, Caprylyl Glycol, Sclerotium Gum, Fragrance, Mica, Titanium Dioxide, Methylparaben, Disodium EDTA, Ethylparaben, Propylparaben

QUESTIONS?

Call 1-800-RoC-1964 (1-800-762-1964); Outside US, dial collect 215-273-8755, or visit ww.rocskincare.com